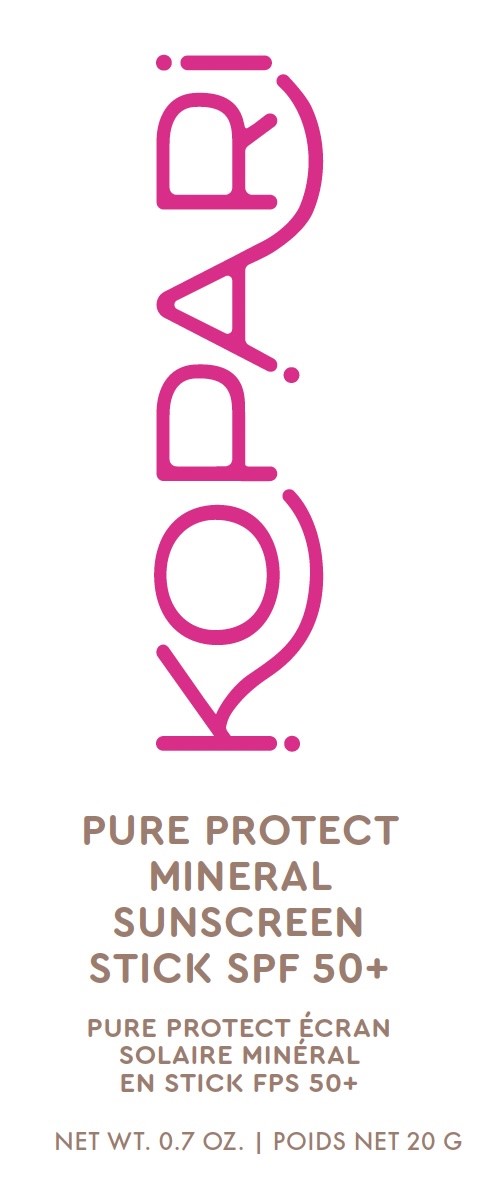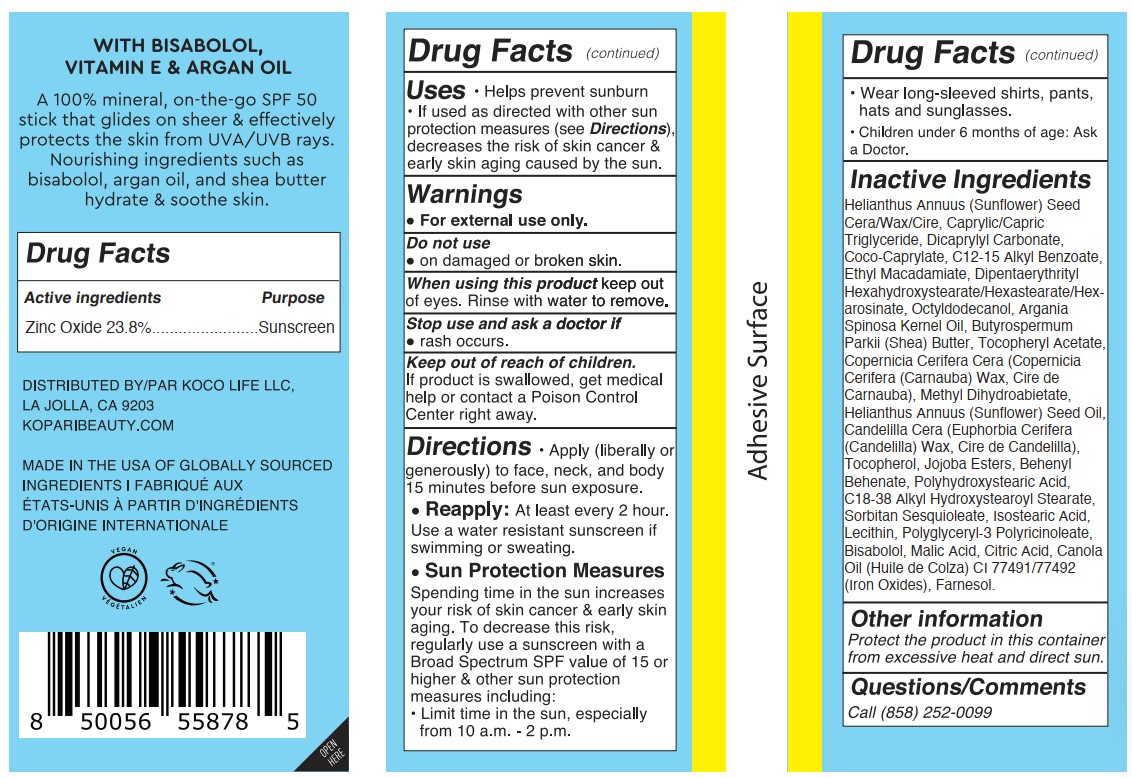 DRUG LABEL: Pure Protect Mineral Sunscreen Stick SPF50
NDC: 84130-010 | Form: STICK
Manufacturer: Koco Life LLC
Category: otc | Type: HUMAN OTC DRUG LABEL
Date: 20240923

ACTIVE INGREDIENTS: ZINC OXIDE 23.8 g/100 g
INACTIVE INGREDIENTS: LEVOMENOL; CANOLA OIL; TOCOPHEROL; POLYGLYCERYL-3 PENTARICINOLEATE; FERROUS OXIDE; BEHENYL BEHENATE; DIPENTAERYTHRITYL HEXAHYDROXYSTEARATE; FARNESOL; POLYHYDROXYSTEARIC ACID STEARATE; SORBITAN SESQUIOLEATE; ETHYL MACADAMIATE; HELIANTHUS ANNUUS SEED WAX; ALKYL (C12-15) BENZOATE; .ALPHA.-TOCOPHEROL ACETATE; MEDIUM-CHAIN TRIGLYCERIDES; CARNAUBA WAX; METHYL DIHYDROABIETATE; MALIC ACID; OCTYLDODECANOL; SHEA BUTTER; CITRIC ACID MONOHYDRATE; DICAPRYLYL CARBONATE; ARGAN OIL; CANDELILLA WAX; LECITHIN, SOYBEAN; C18-38 ALKYL HYDROXYSTEAROYL STEARATE; ISOSTEARIC ACID; COCO-CAPRYLATE; SUNFLOWER OIL; JOJOBA OIL

Pure Protect Mineral Sunscreen Stick SPF50+

Active ingredients

Zinc Oxide 23.8%

Purpose

Zinc Oxide 23.8%................Sunscreen

Uses

- Helps prevent sunburn
- If used as directed with other sun protection measures (see Directions), decreases the risk of skin cancer & early skin aging caused by the sun.

Warnings

For external use only.

Do not use

- on damaged or broken skin.

When using this product keep out of eyes. Rinse with water to remove.

Stop use and ask a doctor if

- rash occurs.

Keep out of reach of children. If product is swallowed, get medical help or contact a Poison Control Center right away.

Directions

- Apply (liberally or generously) to face, neck, and body 15 minutes before sun exposure.
- Reapply: At least every 2 hour. Use a water resistant sunscreen if swimming or sweating.
- Sun Protection Measures
- Spending time in the sun increases your risk of skin cancer & early skin aging. To decrease this risk, regularly use a sunscreen with a Broad Spectrum SPF value of 15 or higher & other sun protection measures including:
- Limit time in the sun, especially from 10 a.m. - 2 p.m.
- Wear long-sleeved shirts, pants, hats and sunglasses.
- Children under 6 months of age: Ask a Doctor.

Inactive ingredients

Helianthus Annuus (Sunflower) Seed Cera/Wax/Cire, Caprylic/Capric Triglyceride, Dicaprylyl Carbonate, Coco-Caprylate, C12-15 Alkyl Benzoate, Ethyl Macadamiate, Dipentaerythrityl Hexahydroxystearate/Hexastearate/Hexarosinate, Octyldodecanol, Argania Spinosa Kernel Oil, Butyrospermum Parkii (Shea) Butter, Tocopheryl Acetate, Copernicia Cerifera Cera (Copernicia Cerifera (Carnauba) Wax, Cire de Carnauba), Methyl Dihydroabietate, Helianthus Annuus (Sunflower) Seed Oil, Candelilla Cera (Euphorbia Cerifera (Candelilla) Wax, Cire de Candelilla), Tocopherol, Jojoba Esters, Behenyl Behenate, Polyhydroxystearic Acid, C18-38 Alkyl Hydroxystearoyl Stearate, Sorbitan Sesquioleate, Isostearic Acid, Lecithin, Polyglyceryl-3 Polyricinoleate, Bisabolol, Malic Acid, Citric Acid, Canola Oil (Huile de Colza) CI 77491/77492 (Iron Oxides), Farnesol

Other information

Protect the product in this container from excessive heat and direct sun.

Questions/Comments

Call (858) 252-0099

PACKAGE LABEL

Kopari

Pure Protect

Mineral

Sunscreen

Stick SPF 50+

Pure Protect Ecran

Solaire Mineral

En Stick FPS 50+

Net Wt. 0.7 oz. | Poids Net 20 G